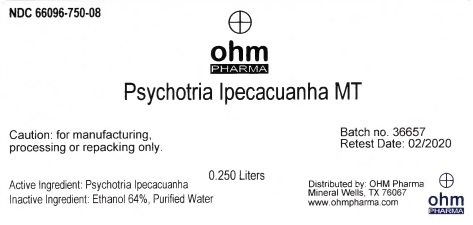 DRUG LABEL: Psychotria Ipecacuanha MT
NDC: 66096-750 | Form: TINCTURE
Manufacturer: OHM PHARMA INC.
Category: homeopathic | Type: HUMAN OTC DRUG LABEL
Date: 20211229

ACTIVE INGREDIENTS: CARAPICHEA IPECACUANHA WHOLE 1 [hp_X]/0.25 L
INACTIVE INGREDIENTS: ALCOHOL; WATER

Psychotria Ipecacuanha MT

Active ingredient: Psychotria Ipecacuanha MT

WARNINGS

Caution: for manufacturing,

processing or repacking only.

Inactive Ingredient: Ethanol 64%, Purified Water

QUESTIONS

Distributed by: OHM Pharma

Mineral Wells, TX 76067

www.ohmpharma.com

PACKAGE LABEL

NDC: 66096-750-08

ohm

PHARMA

Psychotria Ipecacuanha MT

0.250 Liters

Caution: for manufacturing,

processing or repacking only.

Batch no. 36657

Retest Date: 02/2020

Active Ingredient: Psychotria Ipecacuanha

Inactive Ingredient: Ethanol 64%, Purified Water

Distributed by: OHM Pharma

Mineral Wells, TX 76067

www.ohmpharma.com